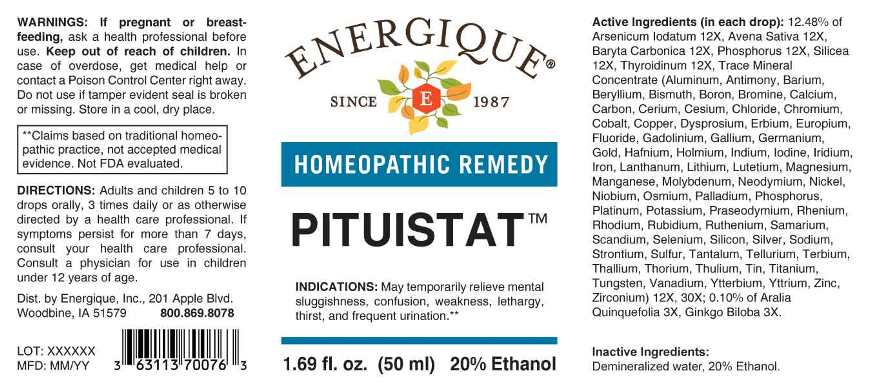 DRUG LABEL: Pituistat
NDC: 44911-0266 | Form: LIQUID
Manufacturer: Energique, Inc.
Category: homeopathic | Type: HUMAN OTC DRUG LABEL
Date: 20230821

ACTIVE INGREDIENTS: AMERICAN GINSENG 3 [hp_X]/1 mL; GINKGO 3 [hp_X]/1 mL; ARSENIC TRIIODIDE 12 [hp_X]/1 mL; AVENA SATIVA FLOWERING TOP 12 [hp_X]/1 mL; BARIUM CARBONATE 12 [hp_X]/1 mL; PHOSPHORUS 12 [hp_X]/1 mL; SILICON DIOXIDE 12 [hp_X]/1 mL; THYROID 12 [hp_X]/1 mL; ALUMINUM 12 [hp_X]/1 mL; ANTIMONY 12 [hp_X]/1 mL; BARIUM 12 [hp_X]/1 mL; BERYLLIUM 12 [hp_X]/1 mL; BISMUTH 12 [hp_X]/1 mL; BORON 12 [hp_X]/1 mL; BROMINE 12 [hp_X]/1 mL; CALCIUM 12 [hp_X]/1 mL; ACTIVATED CHARCOAL 12 [hp_X]/1 mL; CERIUM 12 [hp_X]/1 mL; CESIUM 12 [hp_X]/1 mL; CHLORIDE ION 12 [hp_X]/1 mL; CHROMIUM 12 [hp_X]/1 mL; COBALT 12 [hp_X]/1 mL; COPPER 12 [hp_X]/1 mL; DYSPROSIUM 12 [hp_X]/1 mL; ERBIUM 12 [hp_X]/1 mL; EUROPIUM 12 [hp_X]/1 mL; FLUORIDE ION 12 [hp_X]/1 mL; GADOLINIUM 12 [hp_X]/1 mL; GALLIUM 12 [hp_X]/1 mL; GERMANIUM 12 [hp_X]/1 mL; GOLD 12 [hp_X]/1 mL; HAFNIUM 12 [hp_X]/1 mL; HOLMIUM 12 [hp_X]/1 mL; INDIUM 12 [hp_X]/1 mL; IODINE 12 [hp_X]/1 mL; IRIDIUM 12 [hp_X]/1 mL; IRON 12 [hp_X]/1 mL; LANTHANUM 12 [hp_X]/1 mL; LITHIUM 12 [hp_X]/1 mL; LUTETIUM 12 [hp_X]/1 mL; MAGNESIUM 12 [hp_X]/1 mL; MANGANESE 12 [hp_X]/1 mL; MOLYBDENUM 12 [hp_X]/1 mL; NEODYMIUM 12 [hp_X]/1 mL; NICKEL 12 [hp_X]/1 mL; NIOBIUM 12 [hp_X]/1 mL; OSMIUM 12 [hp_X]/1 mL; PALLADIUM 12 [hp_X]/1 mL; PLATINUM 12 [hp_X]/1 mL; POTASSIUM 12 [hp_X]/1 mL; PRASEODYMIUM 12 [hp_X]/1 mL; RHENIUM 12 [hp_X]/1 mL; RHODIUM 12 [hp_X]/1 mL; RUBIDIUM 12 [hp_X]/1 mL; RUTHENIUM 12 [hp_X]/1 mL; SAMARIUM 12 [hp_X]/1 mL; SCANDIUM 12 [hp_X]/1 mL; SELENIUM 12 [hp_X]/1 mL; SILICON 12 [hp_X]/1 mL; SILVER 12 [hp_X]/1 mL; SODIUM 12 [hp_X]/1 mL; STRONTIUM 12 [hp_X]/1 mL; SULFUR 12 [hp_X]/1 mL; TANTALUM 12 [hp_X]/1 mL; TELLURIUM 12 [hp_X]/1 mL; TERBIUM 12 [hp_X]/1 mL; THALLIUM 12 [hp_X]/1 mL; THORIUM 12 [hp_X]/1 mL; THULIUM 12 [hp_X]/1 mL; TIN 12 [hp_X]/1 mL; TITANIUM 12 [hp_X]/1 mL; TUNGSTEN 12 [hp_X]/1 mL; VANADIUM 12 [hp_X]/1 mL; YTTERBIUM 12 [hp_X]/1 mL; YTTRIUM 12 [hp_X]/1 mL; ZINC 12 [hp_X]/1 mL; ZIRCONIUM 12 [hp_X]/1 mL
INACTIVE INGREDIENTS: WATER; ALCOHOL

DRUG FACTS:

ACTIVE INGREDIENTS:

(in each drop): 12.48% of , Arsenicum Iodatum 12X, Avena Sativa 12X, Baryta Carbonica 12X, Phosphorus 12X, Silicea 12X, Thyroidinum (Suis) 12X, Aluminum 12X, 30X, Antimony 12X, 30X, Barium 12X, 30X , Beryllium 12X, 30X , Bismuth 12X, 30X, Boron 12X, 30X, Bromine 12X, 30X, Calcium 12X, 30X, Carbon 12X, 30X, Cerium 12X, 30X, Cesium 12X, 30X , Chloride 12X, 30X , Chromium 12X, 30X, Cobalt 12X, 30X, Copper 12X, 30X, Dysprosium 12X, 30X, Erbium 12X, 30X, Europium 12X, 30X, Fluoride 12X, 30X, Gadolinium 12X, 30X, Gallium 12X, 30X, Germanium 12X, 30X, Gold 12X, 30X, Hafnium 12X, 30X, Holmium 12X, 30X, Indium 12X, 30X, Iodine 12X, 30X, Iridium 12X, 30X, Iron 12X, 30X, Lanthanum 12X, 30X, Lithium 12X, 30X, Lutetium 12X, 30X, Magnesium 12X, 30X, Manganese 12X, 30X, Molybdenum 12X, 30X, Neodymium 12X, 30X, Nickel 12X, 30X, Niobium 12X, 30X, Osmium 12X, 30X, Palladium 12X, 30X, Phosphorus 12X, 30X, Platinum 12X, 30X, Potassium 12X, 30X, Praseodymium 12X, 30X, Rhenium 12X, 30X, Rhodium 12X, 30X, Rubidium 12X, 30X, Ruthenium 12X, 30X, Samarium 12X, 30X, Scandium 12X, 30X, Selenium 12X, 30X, Silicon 12X, 30X, Silver 12X, 30X, Sodium 12X, 30X, Strontium 12X, 30X, Sulfur 12X, 30X, Tantalum 12X, 30X, Tellurium 12X, 30X, Terbium 12X, 30X, Thallium 12X, 30X, Thorium 12X, 30X, Thulium 12X, 30X, Tin 12X, 30X, Titanium 12X, 30X, Tungsten 12X, 30X, Vanadium 12X, 30X, Ytterbium 12X, 30X, Yttrium 12X, 30X, Zinc 12X, 30X, Zirconium 12X, 30X; 0.10% of Aralia Quinquefolia 3X, Ginkgo Biloba 3X.

INDICATIONS:

For temporarily relieve mental sluggishness, confusion, weakness, lethargy, thirst, and frequent urination.

**Claims based upon traditional homeopathic practice, not accepted medical evidence. Not FDA evaluated.

WARNINGS:

If pregnant or breast-feeding, ask a health professional before use.

Keep out of reach of children. In case of overdose, get medical help or contact a Poison Control Center right away.

Do not use if tamper evident seal is broken or missing. Store in a cool, dry place.

KEEP OUT OF REACH OF CHILDREN:

In case of overdose, get medical help or contact a Poison Control Center right away.

DIRECTIONS:

Adults and children 5 to 10 drops orally, 3 times daily or as otherwise directed by a health care professional. If symptoms persist for more than 7 days, consult your health care professional.

Consult a physician for use in children under 12 years of age.

INDICATIONS:

For temporarily relieve mental sluggishness, confusion, weakness, lethargy, thirst, and frequent urination.

**Claims based upon traditional homeopathic practice, not accepted medical evidence. Not FDA evaluated.

INACTIVE INGREDIENTS:

Demineralized water, 20% Ethanol.

QUESTIONS:

Dist. by Energique, Inc.

201 Apple Blvd.

Woodbine, IA 51579 800.869.8078

PACKAGE LABEL DISPLAY:

ENERGIQUE

SINCE 1987

HOMEOPATHIC REMEDY

PITUISTAT

1.69 fl. oz. (50 ml)